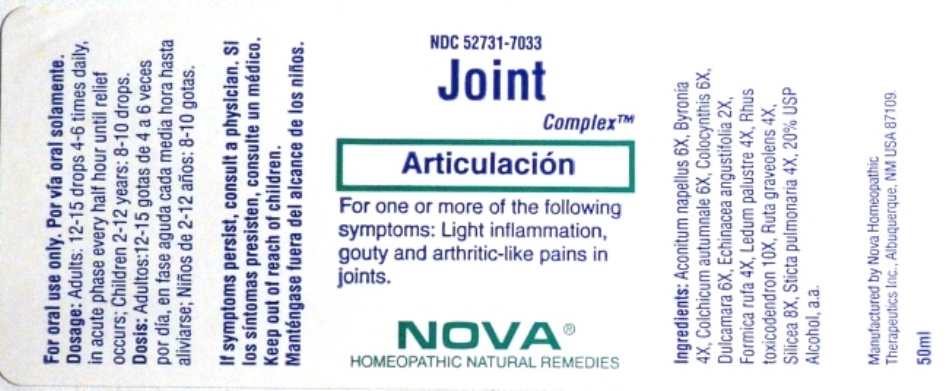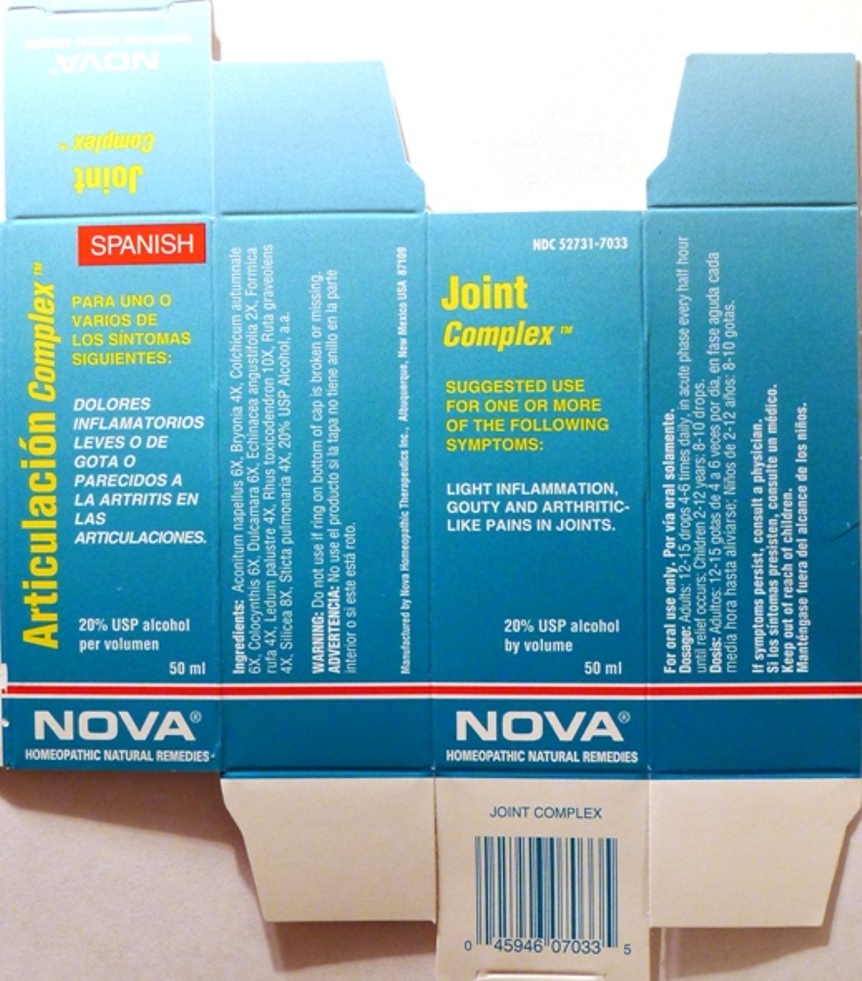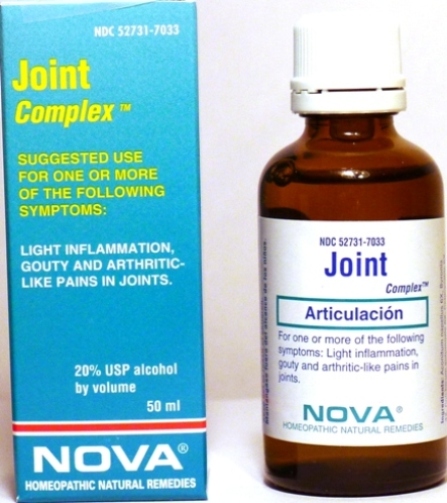 DRUG LABEL: Joint Complex
NDC: 52731-7033 | Form: LIQUID
Manufacturer: Nova Homeopathic Therapeutics, Inc.
Category: homeopathic | Type: HUMAN OTC DRUG LABEL
Date: 20110601

ACTIVE INGREDIENTS: ACONITUM NAPELLUS 6 [hp_X]/1 mL; BRYONIA ALBA ROOT 4 [hp_X]/1 mL; COLCHICUM AUTUMNALE BULB 6 [hp_X]/1 mL; CITRULLUS COLOCYNTHIS FRUIT PULP 6 [hp_X]/1 mL; SOLANUM DULCAMARA STEM 6 [hp_X]/1 mL; ECHINACEA ANGUSTIFOLIA 2 [hp_X]/1 mL; FORMICA RUFA 4 [hp_X]/1 mL; LEDUM PALUSTRE TWIG 4 [hp_X]/1 mL; TOXICODENDRON PUBESCENS LEAF 10 [hp_X]/1 mL; RUTA GRAVEOLENS FLOWERING TOP 4 [hp_X]/1 mL; SILICON DIOXIDE 8 [hp_X]/1 mL; LOBARIA PULMONARIA 4 [hp_X]/1 mL
INACTIVE INGREDIENTS: ALCOHOL

Joint Complex

Purpose:

Suggested use for one or more of the following symptoms:
Light inflammation, gouty and arthritic-like pains in joints.

Usage and Dosage:

For oral use only.

DOSAGE AND ADMINISTRATION

Adults:
In Acute Phase:
12-15 drops, every half hour until relief occurs
When Relief Occurs:
12-15 drops, 4-6 times per day
Children 2-12 years:
8-10 drops, 4-6 times per day

Warnings:

Keep out of reach of children.

WARNINGS

If symptoms persist, consult a physician.
Do not use if ring on bottom of cap is broken or missing.

Active Ingredients:

Aconitum napellus 6X, Bryonia 4X, Colchicum autumnale 6X, Colocynthis 6X, Dulcamara 6X, Echinacea angustifolia 2X, Formica 4X, Ledum Palustre 4X, Rhus toxicodendron 10X, Ruta graveolens 4X, Silicea 8X, Sticta pulmonaria 4X

Inactive Ingredients:

Alcohol, 20% USP

QUESTIONS

Manufactured by Nova Homeopathic Therapeutics Inc., Albuquerque, New Mexico USA 87109
1-800-225-8094

PACKAGE LABEL

Joint Complex Product

Joint Complex Bottle Label

Joint Complex Box